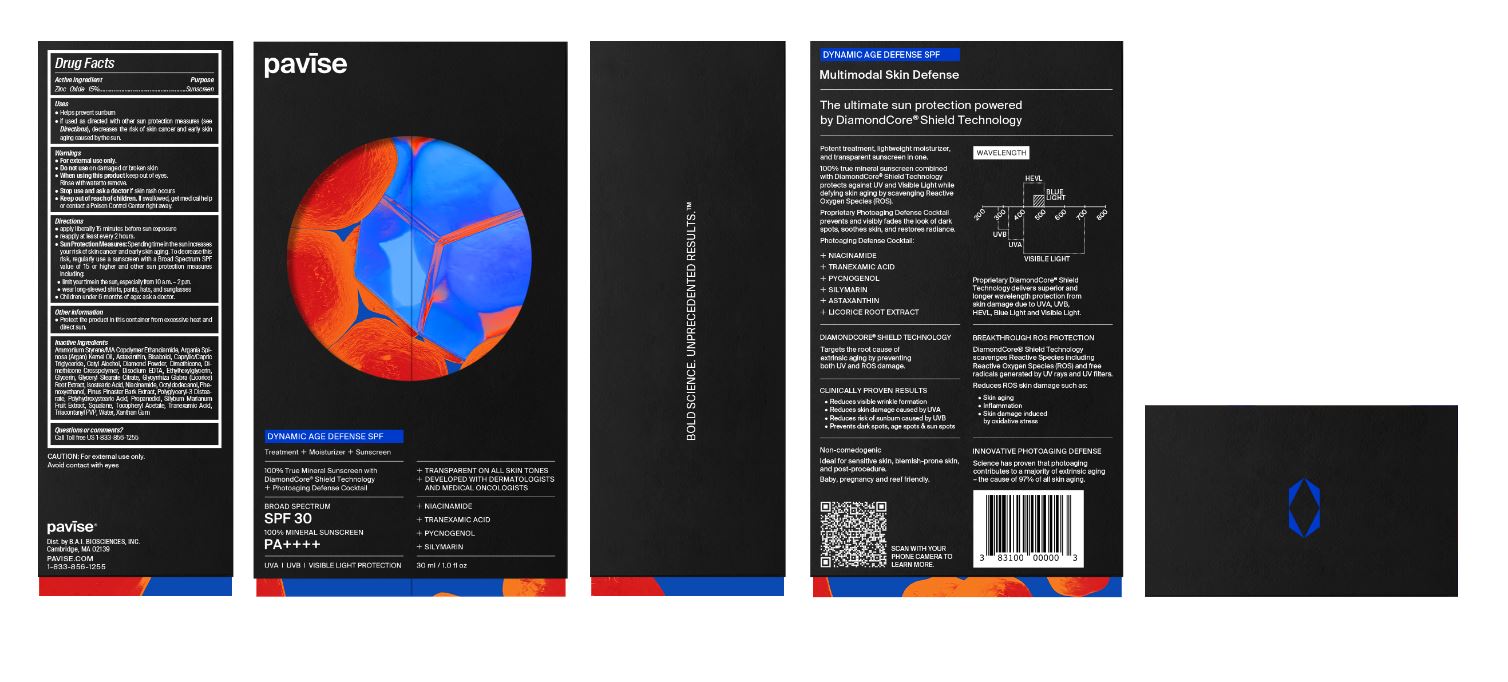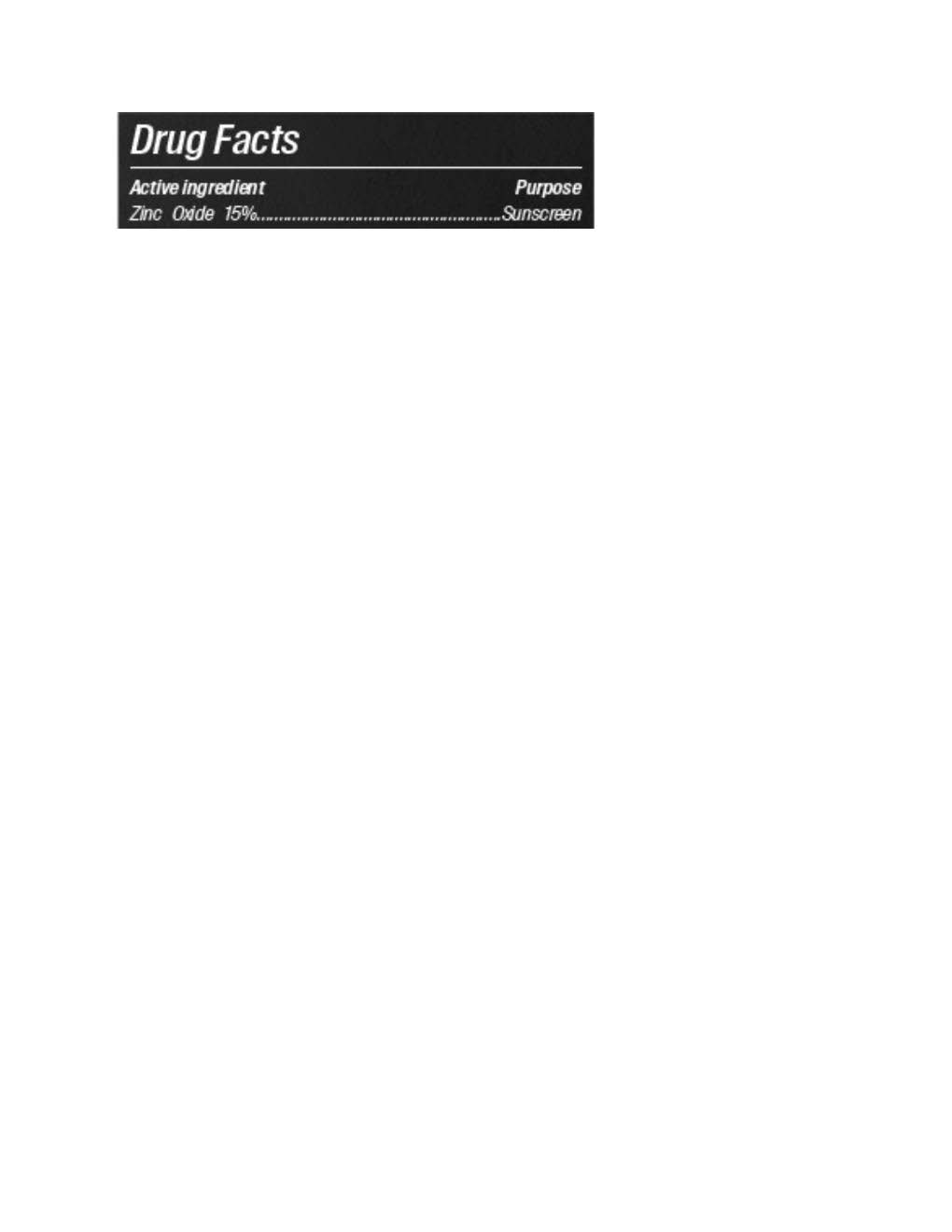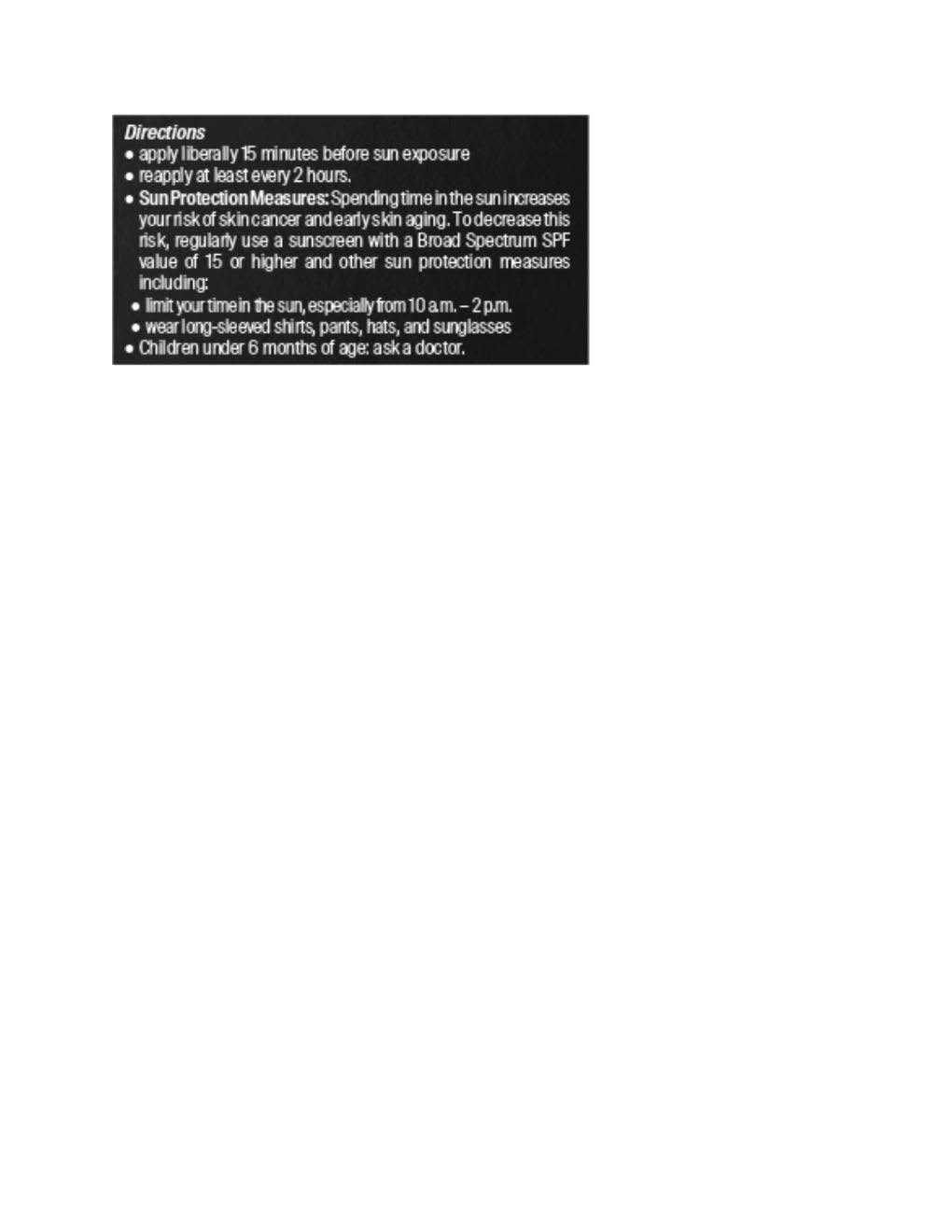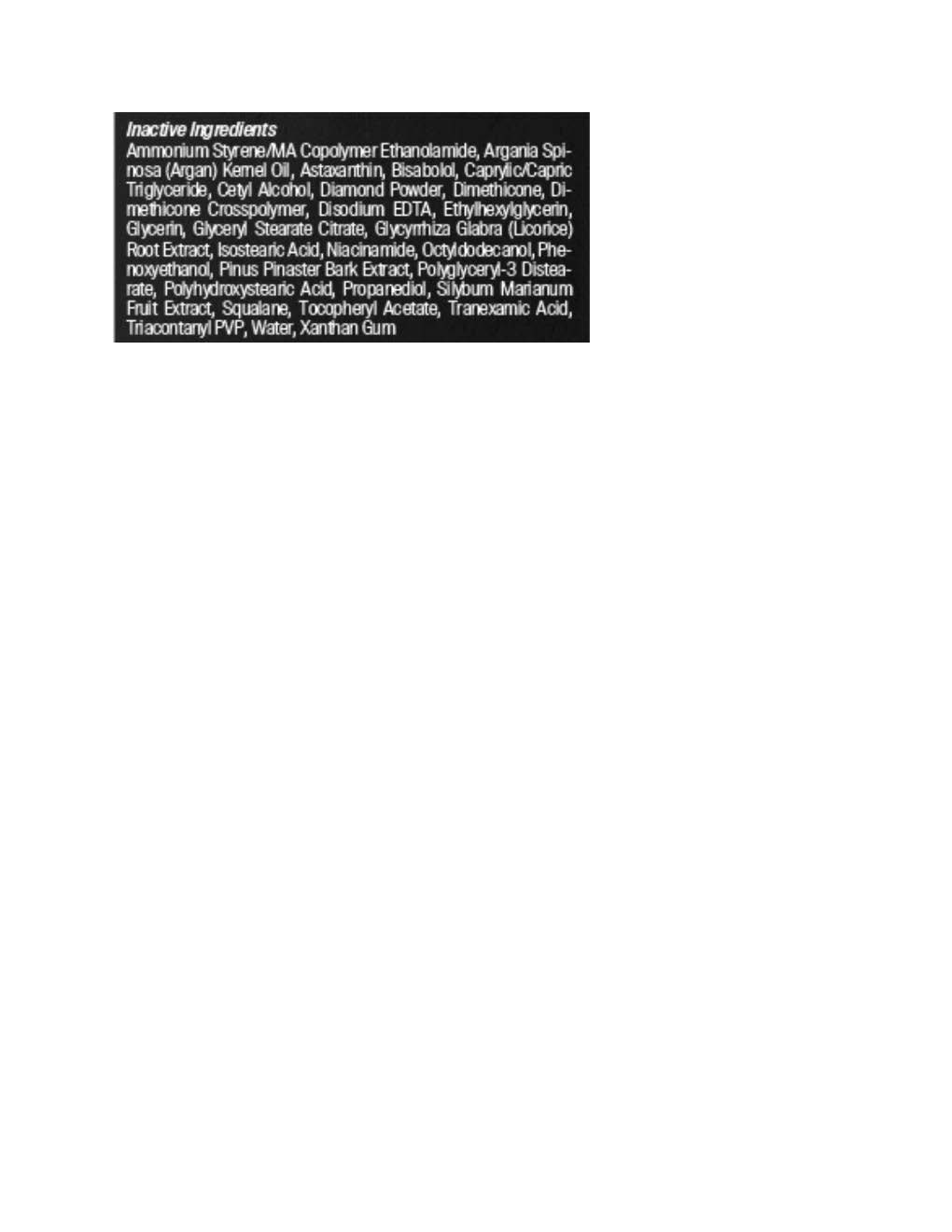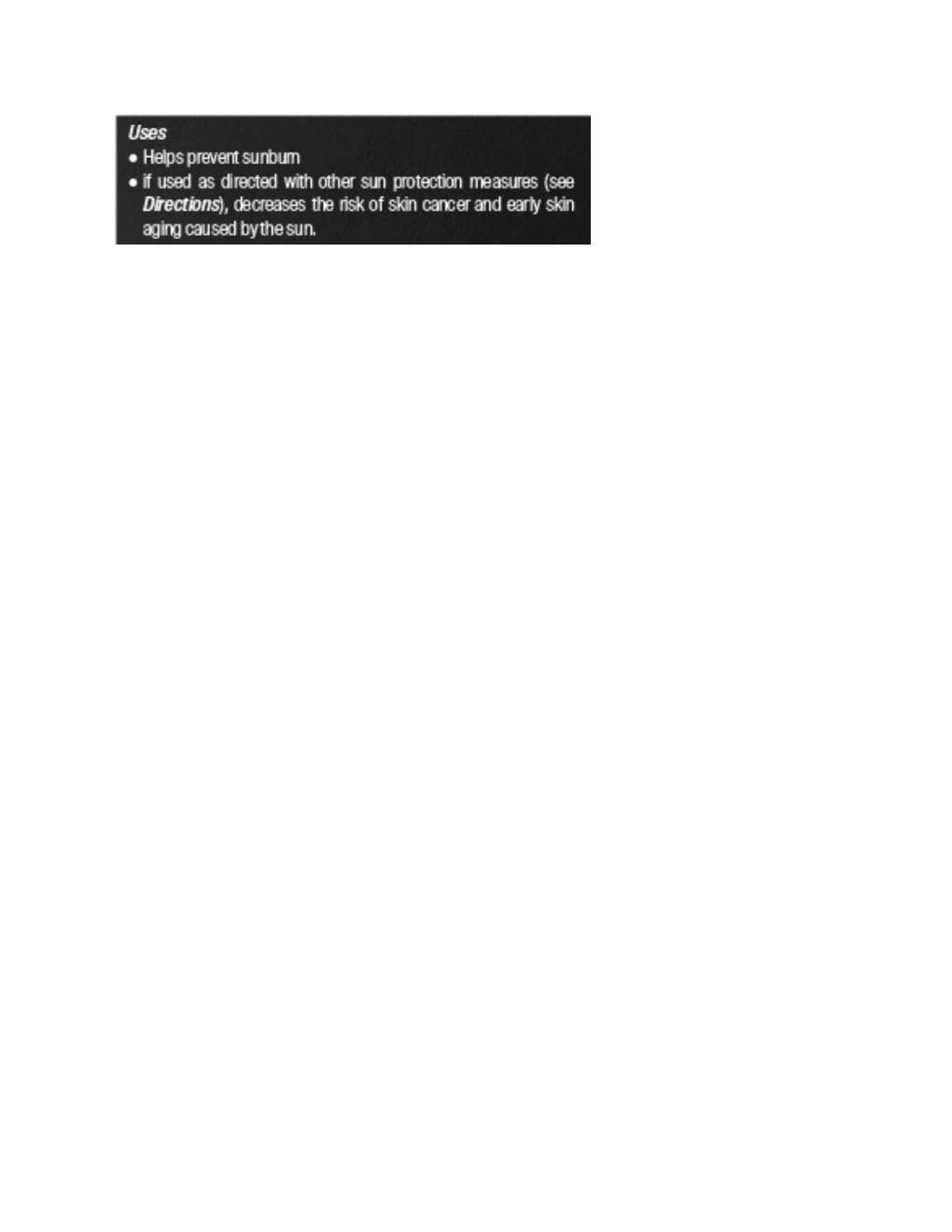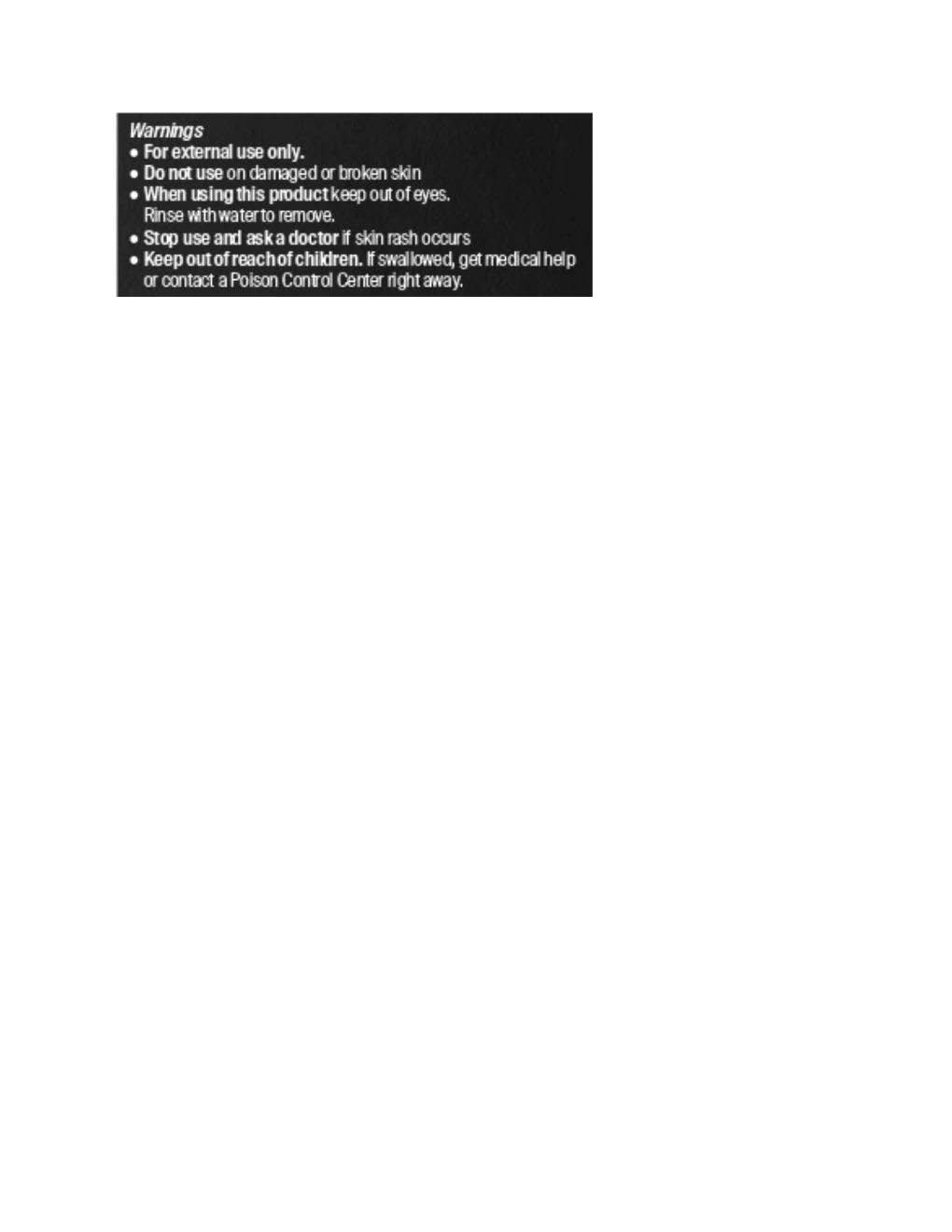 DRUG LABEL: pavise Dynamic Age Defense
NDC: 83100-1720 | Form: LOTION
Manufacturer: B.A.I BIOSCIENCES, INC
Category: otc | Type: HUMAN OTC DRUG LABEL
Date: 20250924

ACTIVE INGREDIENTS: ZINC OXIDE 174 mg/1 mL
INACTIVE INGREDIENTS: ISOSTEARIC ACID; GLYCERYL STEARATE CITRATE; XANTHAN GUM; .ALPHA.-BISABOLOL, (+)-; ASTAXANTHIN; PINUS PINASTER WOOD; PROPANEDIOL; CETYL ALCOHOL; OCTYLDODECANOL; GLYCYRRHIZA GLABRA; PHENOXYETHANOL; SILYBUM MARIANUM SEED; TRANEXAMIC ACID; GLYCERIN; DIMETHICONE; WATER; NIACINAMIDE; POLYHYDROXYSTEARIC ACID (2300 MW); DIMETHICONE CROSSPOLYMER (450000 MPA.S AT 12% IN CYCLOPENTASILOXANE); ETHYLHEXYLGLYCERIN; DISODIUM ETHYLENEDIAMINEDIACETATE; POLYGLYCERYL-3 DISTEARATE; ARGANIA SPINOSA SEED; SQUALANE; TRIACONTANYL PVP (WP-660); DIAMOND

pavise Dynamic Age Defense